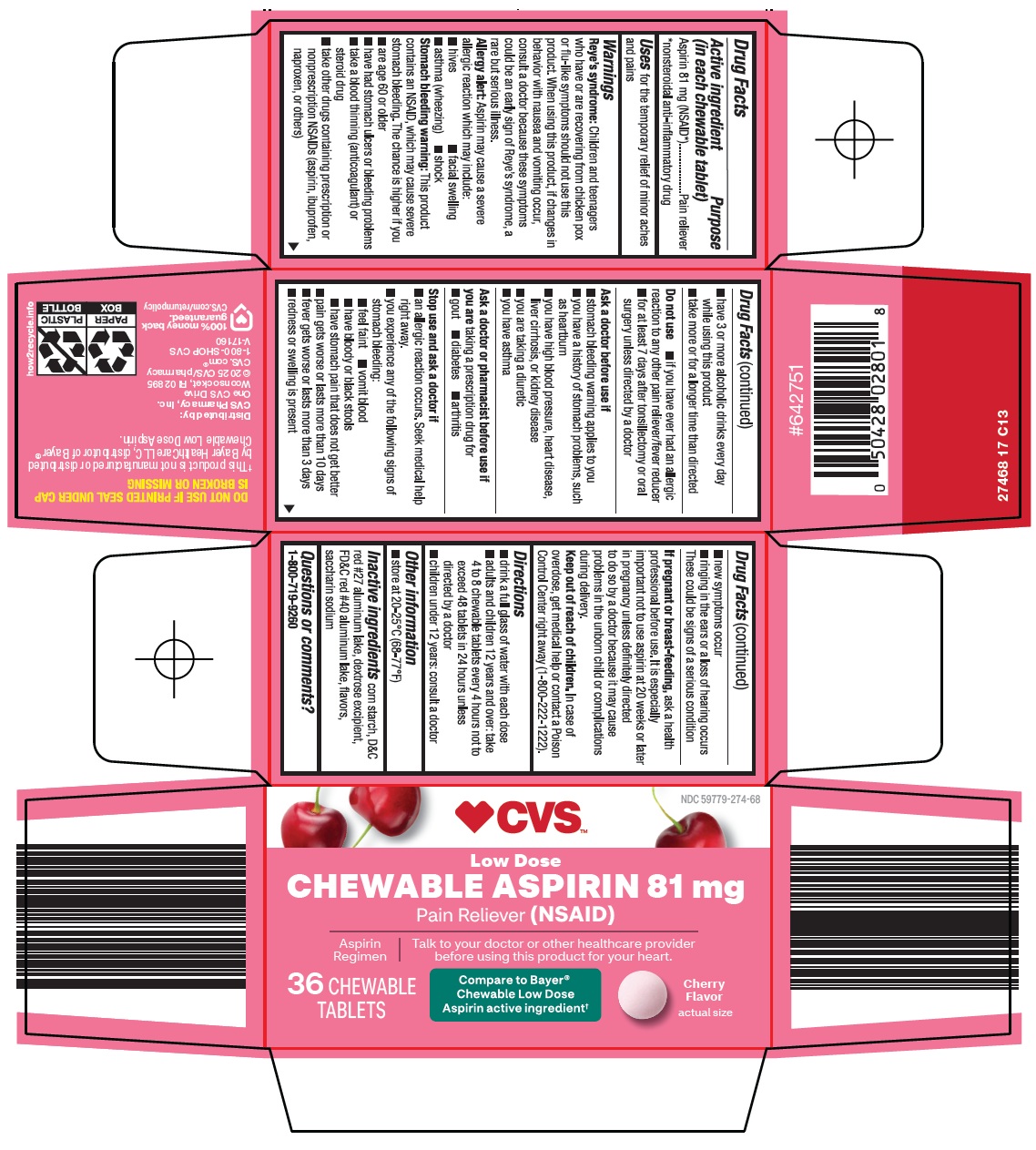 DRUG LABEL: aspirin
NDC: 59779-274 | Form: TABLET, CHEWABLE
Manufacturer: CVS Pharmacy
Category: otc | Type: HUMAN OTC DRUG LABEL
Date: 20260226

ACTIVE INGREDIENTS: ASPIRIN 81 mg/1 1
INACTIVE INGREDIENTS: STARCH, CORN; D&C RED NO. 27 ALUMINUM LAKE; FD&C RED NO. 40 ALUMINUM LAKE; SACCHARIN SODIUM

CVS Pharmacy, Inc. Chewable Aspirin 81 mg Drug Facts

Active ingredient (in each chewable tablet)

Aspirin 81 mg (NSAID*)

*nonsteroidal anti-inflammatory drug

Purpose

Pain reliever

Uses

for the temporary relief of minor aches and pains

Warnings

Reye’s syndrome: Children and teenagers who have or are recovering from chicken pox or flu-like symptoms should not use this product. When using this product, if changes in behavior with nausea and vomiting occur, consult a doctor because these symptoms could be an early sign of Reye’s syndrome, a rare but serious illness.

Allergy alert: Aspirin may cause a severe allergic reaction which may include:

- hives
- facial swelling
- asthma (wheezing)
- shock

Stomach bleeding warning: This product contains an NSAID, which may cause severe stomach bleeding. The chance is higher if you

- are age 60 or older
- have had stomach ulcers or bleeding problems
- take a blood thinning (anticoagulant) or steroid drug
- take other drugs containing prescription or nonprescription NSAIDs (aspirin, ibuprofen, naproxen, or others)
- have 3 or more alcoholic drinks every day while using this product
- take more or for a longer time than directed

Do not use

- if you have ever had an allergic reaction to any other pain reliever/fever reducer
- for at least 7 days after tonsillectomy or oral surgery unless directed by a doctor

Ask a doctor before use if

- stomach bleeding warning applies to you
- you have a history of stomach problems, such as heartburn
- you have high blood pressure, heart disease, liver cirrhosis, or kidney disease
- you are taking a diuretic
- you have asthma

Ask a doctor or pharmacist before use if you are

taking a prescription drug for

- gout
- diabetes
- arthritis

Stop use and ask a doctor if

- an allergic reaction occurs. Seek medical help right away.
- you experience any of the following signs of stomach bleeding:
  - feel faint
  - vomit blood
  - have bloody or black stools
  - have stomach pain that does not get better
- pain gets worse or lasts more than 10 days
- fever gets worse or lasts more than 3 days
- redness or swelling is present
- new symptoms occur
- ringing in the ears or a loss of hearing occurs

These could be signs of a serious condition

If pregnant or breast-feeding,

ask a health professional before use. It is especially important not to use aspirin at 20 weeks or later in pregnancy unless definitely directed to do so by a doctor because it may cause problems in the unborn child or complications during delivery.

Keep out of reach of children.

In case of overdose, get medical help or contact a Poison Control Center right away (1-800-222-1222).

Directions

- drink a full glass of water with each dose
- adults and children 12 years and over: take 4 to 8 chewable tablets every 4 hours not to exceed 48 tablets in 24 hours unless directed by a doctor
- children under 12 years: consult a doctor

Other information

- store at 20-25°C (68-77°F)

Inactive ingredients

corn starch, D&C red #27 aluminum lake, dextrose excipient, FD&C red #40 aluminum lake, flavors, saccharin sodium

Principal Display Panel

CVS™

Low Dose

CHEWABLE ASPIRIN 81 mg

Pain Reliever (NSAID)

Aspirin Regimen

Talk to your doctor or other healthcare provider before using this product for your heart.

36 CHEWABLE TABLETS

Compare to Bayer® Chewable Low Dose Aspirin active ingredient

Cherry Flavor

actual size